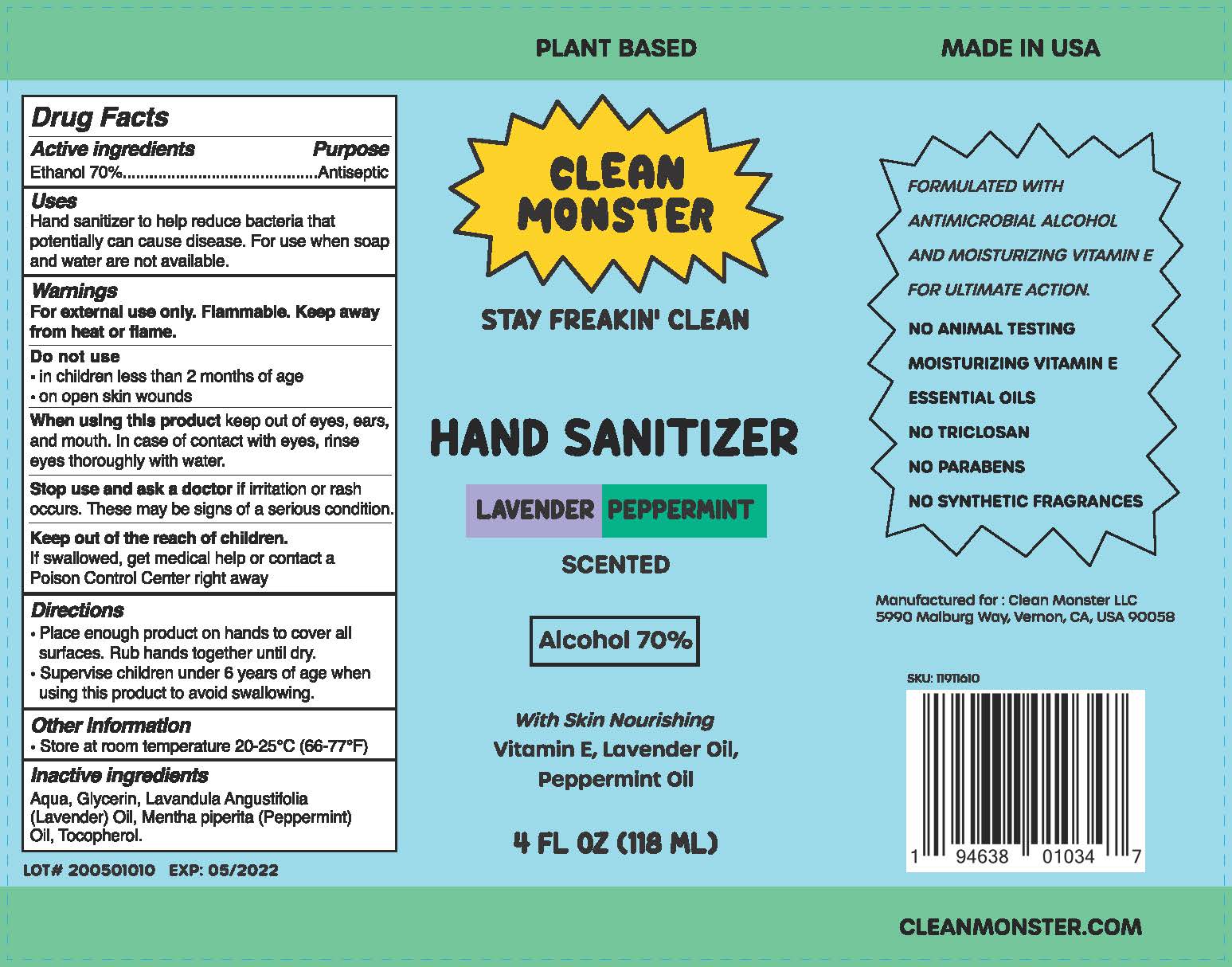 DRUG LABEL: Clean Monster Lavender Peppermint Hand Sanitizer
NDC: 78723-001 | Form: LIQUID
Manufacturer: Clean Monster LLC
Category: otc | Type: HUMAN OTC DRUG LABEL
Date: 20200601

ACTIVE INGREDIENTS: ALCOHOL 70 mL/100 mL
INACTIVE INGREDIENTS: GLYCERIN; WATER; .ALPHA.-TOCOPHEROL, DL-; LAVENDER OIL; PEPPERMINT OIL

ACTIVE INGREDIENT

Ethanol 70%

Purpose:

Antiseptic

Uses:

Hand sanitizer to help reduce bacteria that potentially can cause disease. For use when soap and water are not available.

WARNINGS:

For external use only. Flammable. Keep away from heat or flame.

Do not use

- In children less than 2 months of age
- On open skin wounds

When using this product keep out of eyes, ears, and mouth. In case of contact with eyes, rinse eyes thoroughly with water.

Stop use and ask a doctor if irritation or rash occurs. These may be signs of a serious condition.

Keep out of reach of children. If swallowed, get medical help or contact the Poison Control Center right away.

Directions:

- Place enough product on hands to cover all surfaces. Rub hands together until dry.
- Supervise children under 6 years of age when using this product to avoid swallowing.

STORAGE AND HANDLING

Store at room temperature 20-25 °C (66-77 °F)

Inactive Ingredients:

Aqua, Glycerin, Lavandula Angustifolia (Lavender) Oil, Mentha piperita (Peppermint) Oil, Tocopherol.